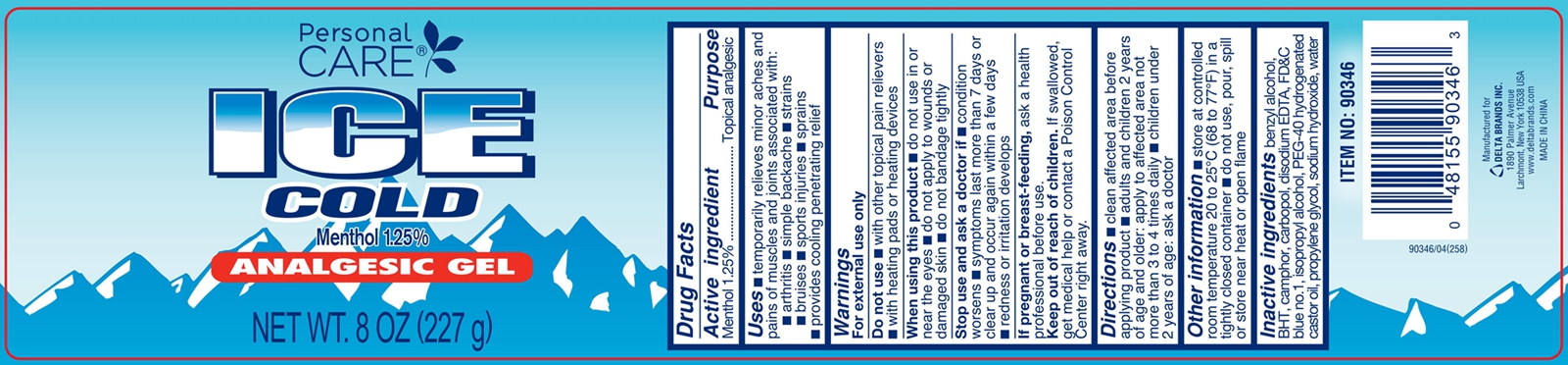 DRUG LABEL: PERSONAL CARE ICE COLD
NDC: 76176-021 | Form: GEL
Manufacturer: NINGBO LIYUAN DAILY CHEMICAL PRODUCTS CO., LTD.
Category: otc | Type: HUMAN OTC DRUG LABEL
Date: 20240101

ACTIVE INGREDIENTS: MENTHOL 1.25 g/100 g
INACTIVE INGREDIENTS: SODIUM HYDROXIDE; PROPYLENE GLYCOL; HYDROGENATED CASTOR OIL; BUTYLATED HYDROXYTOLUENE; WATER; FD&C BLUE NO. 1; CAMPHOR (SYNTHETIC); BENZYL ALCOHOL; EDETATE DISODIUM; CARBOMER 934; ISOPROPYL ALCOHOL

Active ingredient

Menthol 1.25%

Purpose

Topical analgesic

Uses

temporarily relieves minor muscle aches and pains of muscles and joints associated with:

arthritis, simple backache, strains, bruises, sports injuries, sprains, provides cooling penetrating relief

Warnings

For external use only.

Do not use: with other topical pain relievers, with heating pads or heating devices.

When using this product

do not use in or near the eyes.

do not apply to wounds or damaged skin.

do not bandage tightly.

Stop use and ask a doctor if

condition worsens, symptoms last more than 7 days or clear up and occur again within a few days, redness or irritation develops.

If pregnant or breast-feeding,

ask a health professional before use.

Keep out of reach of children.

If swallowed, get medical help or contact a Poison Control Center right away.

Directions

clean affected area before applying product.

adults and children 2 years of age and older: apply to affected area not more than 3 to 4 times daily.

chidlren under 2 years of age: ask a doctor.

Other information

store at controlled room temperature 20 to 25℃ (68 to 77°F) in a tightly closed container.

do not use, pour, spill or store near heat or open flame.

Inactive ingredients

benzyl alcohol, BHT, camphor, carbopol, disodium EDTA, FD&C blue no.1, isopropyl alcohol, PEG-40 hydrogenated castor oil, propylene glycol, sodium hydroxide, water